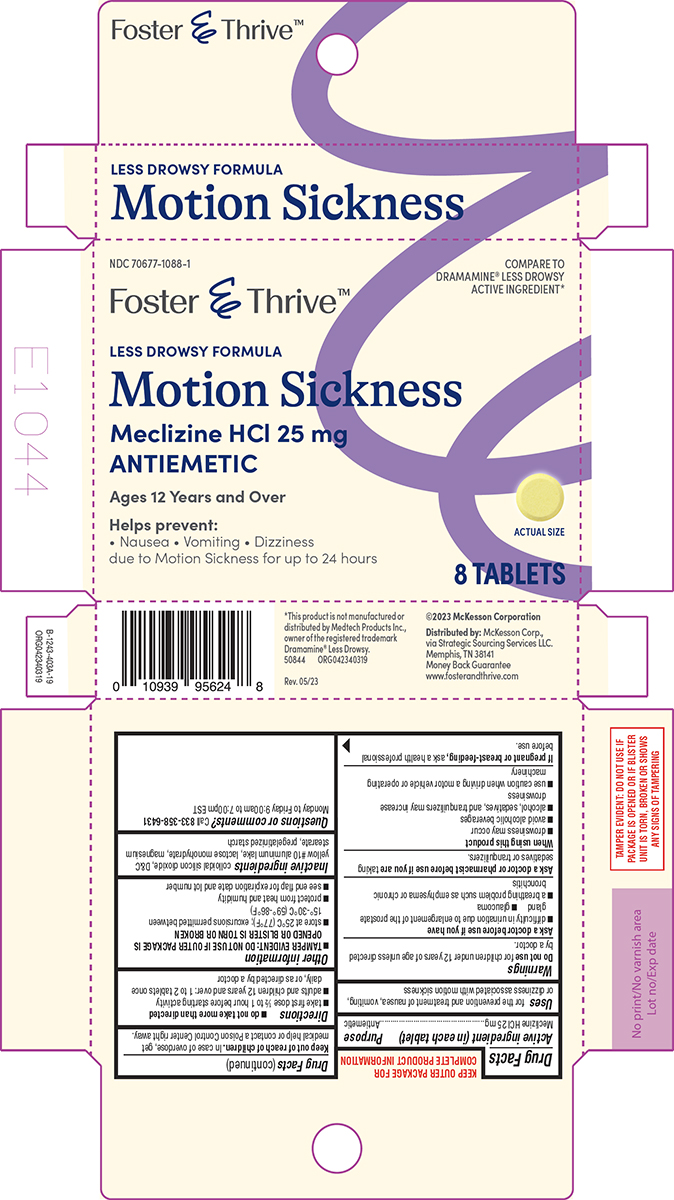 DRUG LABEL: Motion Sickness
NDC: 70677-1088 | Form: TABLET
Manufacturer: Strategic Sourcing Services LLC
Category: otc | Type: HUMAN OTC DRUG LABEL
Date: 20250818

ACTIVE INGREDIENTS: MECLIZINE HYDROCHLORIDE 25 mg/1 1
INACTIVE INGREDIENTS: SILICON DIOXIDE; D&C YELLOW NO. 10 ALUMINUM LAKE; LACTOSE MONOHYDRATE; MAGNESIUM STEARATE; STARCH, CORN

Foster and Thrive 44-403A

Active ingredient (in each tablet)

Meclizine HCl 25 mg

Purpose

Antiemetic

Uses

for the prevention and treatment of nausea, vomiting, or dizziness associated with motion sickness

Warnings

Do not use

for children under 12 years of age unless directed by a doctor.

Ask a doctor before use if you have

- difficulty in urination due to enlargement of the prostate gland
- glaucoma
- a breathing problem such as emphysema or chronic bronchitis

Ask a doctor or pharmacist before use if you are

taking sedatives or tranquilizers.

When using this product

- drowsiness may occur
- avoid alcoholic beverages
- alcohol, sedatives, and tranquilizers may increase drowsiness
- use caution when driving a motor vehicle or operating machinery

If pregnant or breast-feeding,

ask a health professional before use.

Keep out of reach of children.

In case of overdose, get medical help or contact a Poison Control Center right away.

Directions

- do not take more than directed
- take first dose ½ to 1 hour before starting activity
- adults and children 12 years and over: 1 to 2 tablets once daily, or as directed by a doctor

Other information

- TAMPER EVIDENT: DO NOT USE IF OUTER PACKAGE IS OPENED OR BLISTER IS TORN OR BROKEN
- store at 25°C (77°F); excursions permitted between 15°-30°C (59°-86°F)
- protect from heat and humidity
- see end flap for expiration date and lot number

Inactive ingredients

colloidal silicon dioxide, D&C yellow #10 aluminum lake, lactose monohydrate, magnesium stearate, pregelatinized starch

Questions or comments?

Call 833-358-6431 Monday to Friday 9:00am to 7:00pm EST

Principal display panel

NDC 70677-1088-1

Foster & Thrive™

COMPARE TO
DRAMAMINE® LESS DROWSY
ACTIVE INGREDIENT*

LESS DROWSY FORMULA
Motion Sickness
Meclizine HCl 25 mg
ANTIEMETIC

Ages 12 Years and Over

Helps prevent:
• Nausea • Vomiting • Dizziness
due to Motion Sickness for up to 24 hours

ACTUAL SIZE

8 TABLETS

TAMPER EVIDENT: DO NOT USE IF
PACKAGE IS OPENED OR IF BLISTER
UNIT IS TORN, BROKEN OR SHOWS
ANY SIGNS OF TAMPERING

*This product is not manufactured or
distributed by Medtech Products Inc.,
owner of the registered trademark
Dramamine® Less Drowsy.
50844 ORG042340319

Rev. 05/23

©2023 McKesson Corporation

Distributed by: McKesson Corp.,
via Strategic Sourcing Services LLC.
Memphis, TN 38141
Money Back Guarantee
www.fosterandthrive.com

Foster and Thrive 44-403A